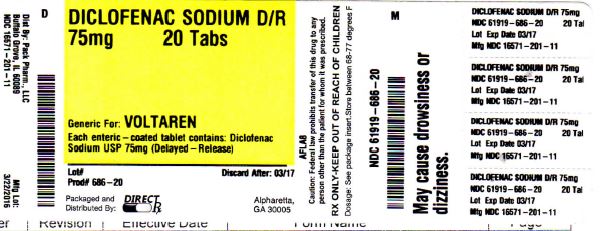 DRUG LABEL: DICLOFENAC SODIUM
NDC: 61919-686 | Form: TABLET, DELAYED RELEASE
Manufacturer: DIRECT RX
Category: prescription | Type: HUMAN PRESCRIPTION DRUG LABEL
Date: 20160421

ACTIVE INGREDIENTS: DICLOFENAC SODIUM 75 mg/1 1
INACTIVE INGREDIENTS: CELLULOSE, MICROCRYSTALLINE; POVIDONE, UNSPECIFIED; TALC; MAGNESIUM STEARATE; METHACRYLIC ACID - ETHYL ACRYLATE COPOLYMER (1:1) TYPE A; POLYETHYLENE GLYCOL, UNSPECIFIED; HYPROMELLOSES; FERRIC OXIDE RED; FERRIC OXIDE YELLOW; CROSCARMELLOSE SODIUM; TITANIUM DIOXIDE; WATER; LACTOSE MONOHYDRATE

DICLOFENAC SODIUM DR 75mg 20 TABS